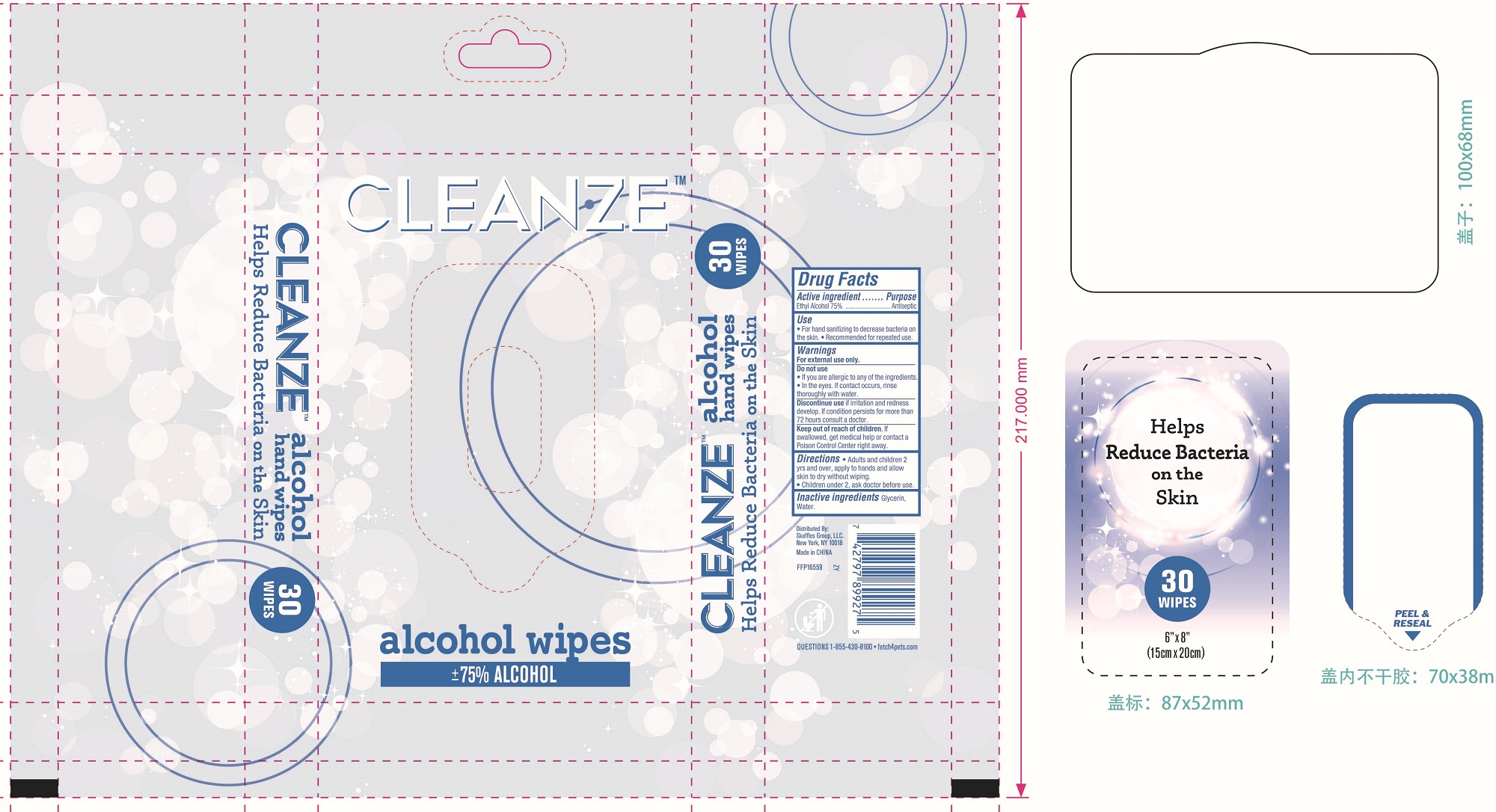 DRUG LABEL: HAND ALCOHOL WIPES
NDC: 77720-015 | Form: CLOTH
Manufacturer: Skaffles Group Limited Liability Company
Category: otc | Type: HUMAN OTC DRUG LABEL
Date: 20201230

ACTIVE INGREDIENTS: ALCOHOL 75 mL/100 mL
INACTIVE INGREDIENTS: WATER; GLYCERIN

77720-015 HAND ALCOHOL WIPES 75%Ethyl Alcohol

Active Ingredient

Ethyl Alcohol 75%

Purpose

Antiseptic

USE

For hand washing to decrease bacteria on the skin.
Recommended for repeated use.

Warning

For external use only. Do not use
. If you are allergic to any of the ingredients.. ln the eyes. If contact occurs, rinse
thoroughly with water.
Discontinue use if irritation and redness develop. If condition persists for more than72 hours consult a doctor.

Keep out of reach of children. lf swallowed, get medical help or contact a Poison Control Center right away.

Directions

Directions● Adults and children 2 yrs and over,
apply to hands and allow skin to dry without wiping.
●Children under 2, ask doctor before use.

Inactive ingredients

Glycerin,Water.